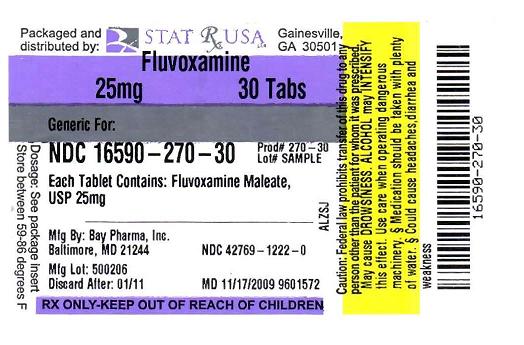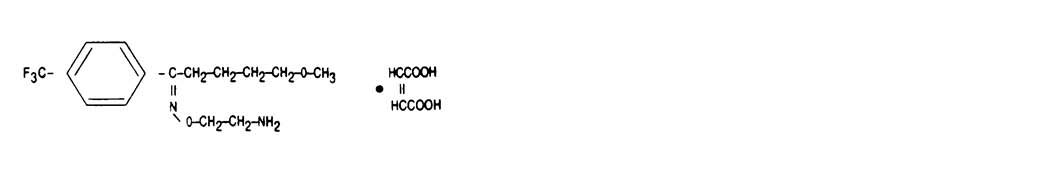 DRUG LABEL: Fluvoxamine Maleate
NDC: 16590-270 | Form: TABLET
Manufacturer: Stat Rx USA
Category: prescription | Type: HUMAN PRESCRIPTION DRUG LABEL
Date: 20091027

ACTIVE INGREDIENTS: FLUVOXAMINE MALEATE 25 mg/1 1

Insert

11. DESCRIPTION

Fluvoxamine maleate is a selective serotonin (5-HT) reuptake inhibitor (SSRI) belonging to the chemical series, the 2-aminoethyl oxime ethers of aralkylketones.

It is chemically designated as 5-methoxy-4′-(trifluoromethyl)valerophenone-(E)-O-(2-aminoethyl)oxime maleate (1:1) and has the empirical formula C15H21O2N2F3•C4H4O4. Its molecular weight is 434.41.

The structural formula is:

Fluvoxamine maleate is a white to off white, odorless, crystalline powder which is sparingly soluble in water, freely soluble in ethanol and chloroform and practically insoluble in diethyl ether.

Fluvoxamine Maleate Tablets are available in 25 mg, 50 mg and 100 mg strengths for oral administration. In addition to the active ingredient, fluvoxamine maleate, each tablet contains the following inactive ingredients: carnauba wax, hydroxypropyl methylcellulose, mannitol, polyethylene glycol, polysorbate 80, pregelatinized starch (potato), silicon dioxide, sodium stearyl fumarate, starch (corn), and titanium dioxide. The 50 mg and 100 mg tablets also contain synthetic iron oxides.

12. CLINICAL PHARMACOLOGY 12.1 Mechanism Of Action

The mechanism of action of fluvoxamine maleate in obsessive compulsive disorder is presumed to be linked to its specific serotonin reuptake inhibition in brain neurons. Fluvoxamine has been shown to be a potent inhibitor of the serotonin reuptake transporter in preclinical studies, both in vitro and in vivo.

12.2 Pharmacodynamics

In in vitro studies, fluvoxamine maleate had no significant affinity for histaminergic, alpha or beta adrenergic, muscarinic, or dopaminergic receptors. Antagonism of some of these receptors is thought to be associated with various sedative, cardiovascular, anticholinergic, and extrapyramidal effects of some psychotropic drugs.

12.3 Pharmacokinetics

Absorption: The absolute bioavailability of fluvoxamine maleate is 53%. Oral bioavailability is not significantly affected by food.

In a dose proportionality study involving fluvoxamine maleate at 100, 200 and 300 mg/day for 10 consecutive days in 30 normal volunteers, steady state was achieved after about a week of dosing. Maximum plasma concentrations at steady state occurred within 3-8 hours of dosing and reached concentrations averaging 88, 283 and 546 ng/mL, respectively. Thus, fluvoxamine had nonlinear pharmacokinetics over this dose range, i.e., higher doses of fluvoxamine maleate produced disproportionately higher concentrations than predicted from the lower dose.

Distribution: The mean apparent volume of distribution for fluvoxamine is approximately 25 L/kg, suggesting extensive tissue distribution.

Approximately 80% of fluvoxamine is bound to plasma protein, mostly albumin, over a concentration range of 20 to 2000 ng/mL.

Metabolism: Fluvoxamine maleate is extensively metabolized by the liver; the main metabolic routes are oxidative demethylation and deamination. Nine metabolites were identified following a 5 mg radiolabelled dose of fluvoxamine maleate, constituting approximately 85% of the urinary excretion products of fluvoxamine. The main human metabolite was fluvoxamine acid which, together with its N-acetylated analog, accounted for about 60% of the urinary excretion products. A third metabolite, fluvoxethanol, formed by oxidative deamination, accounted for about 10%. Fluvoxamine acid and fluvoxethanol were tested in an in vitro assay of serotonin and norepinephrine reuptake inhibition in rats; they were inactive except for a weak effect of the former metabolite on inhibition of serotonin uptake (1-2 orders of magnitude less potent than the parent compound). Approximately 2% of fluvoxamine was excreted in urine unchanged. (See DRUG INTERACTIONS [7].)

Elimination: Following a^14C-labelled oral dose of fluvoxamine maleate (5 mg), an average of 94% of drug-related products was recovered in the urine within 71 hours.

The mean plasma half-life of fluvoxamine at steady state after multiple oral doses of 100 mg/day in healthy, young volunteers was 15.6 hours.

Elderly Subjects: In a study of Fluvoxamine Maleate Tablets at 50 and 100 mg comparing elderly (ages 66-73) and young subjects (ages 19-35), mean maximum plasma concentrations in the elderly were 40% higher. The multiple dose elimination half-life of fluvoxamine was 17.4 and 25.9 hours in the elderly compared to 13.6 and 15.6 hours in the young subjects at steady state for 50 and 100 mg doses, respectively. In elderly patients, the clearance of fluvoxamine was reduced by about 50% and, therefore, Fluvoxamine Maleate Tablets should be slowly titrated during initiation of therapy. (See DOSAGE AND ADMINISTRATION [2.3].)

Pediatric Subjects: The multiple-dose pharmacokinetics of fluvoxamine were determined in male and female children (ages 6-11) and adolescents (ages 12-17). Steady-state plasma fluvoxamine concentrations were 2-3 fold higher in children than in adolescents. AUC and Cmax in children were 1.5- to 2.7-fold higher than that in adolescents. (See Table 4.) As in adults, both children and adolescents exhibited nonlinear multiple-dose pharmacokinetics. Female children showed significantly higher AUC (0-12) and Cmax compared to male children and, therefore, lower doses of Fluvoxamine Maleate Tablets may produce therapeutic benefit. (See Table 5.) No gender differences were observed in adolescents. Steady-state plasma fluvoxamine concentrations were similar in adults and adolescents at a dose of 300 mg/day, indicating that fluvoxamine exposure was similar in these two populations. (See Table 4.) Dose adjustment in adolescents (up to the adult maximum dose of 300 mg) may be indicated to achieve therapeutic benefit. (See DOSAGE AND ADMINISTRATION [2.2].)

Hepatic and Renal Disease: A cross study comparison (healthy subjects versus patients with hepatic dysfunction) suggested a 30% decrease in fluvoxamine clearance in association with hepatic dysfunction. The mean minimum plasma concentrations in renally impaired patients (creatinine clearance of 5 to 45 mL/min) after 4 and 6 weeks of treatment (50 mg b.i.d., N=13) were comparable to each other, suggesting no accumulation of fluvoxamine in these patients. (See WARNINGS AND PRECAUTIONS - Use in Patients with Concomitant Illness [5.13].)

INDICATIONS AND USAGE

1. INDICATIONS AND USAGE 1.1 Obsessive-Compulsive Disorder

Fluvoxamine Maleate Tablets are indicated for the treatment of obsessions and compulsions in patients with obsessive compulsive disorder (OCD), as defined in DSM-III-R or DSM-IV. The obsessions or compulsions cause marked distress, are time-consuming, or significantly interfere with social or occupational functioning.

Obsessive compulsive disorder is characterized by recurrent and persistent ideas, thoughts, impulses or images (obsessions) that are ego-dystonic and/or repetitive, purposeful, and intentional behaviors (compulsions) that are recognized by the person as excessive or unreasonable.

The efficacy of Fluvoxamine Maleate Tablets was established in four trials in outpatients with OCD: two 10-week trials in adults, one 10-week trial in pediatric patients (ages 8-17), and one maintenance trial in adults. (See CLINICAL STUDIES [14].)

4. CONTRAINDICATIONS

Coadministration of tizanidine, thioridazine, alosetron, or pimozide with Fluvoxamine Maleate Tablets is contraindicated. (See WARNINGS AND PRECAUTIONS [5.3- 5.6].)

The use of MAOIs concomitantly with or within 14 days of treatment with Fluvoxamine Maleate Tablets is contraindicated. (See WARNINGS AND PRECAUTIONS [5.2].)

ADVERSE REACTIONS

6. ADVERSE REACTIONS 6.1 Adverse Reactions Leading to Treatment Discontinuation

Of the 1087 OCD and depressed patients treated with fluvoxamine maleate in controlled clinical trials in North America, 22% discontinued due to an adverse reaction. Adverse reactions that led to discontinuation in at least 2% of fluvoxamine maleate-treated patients in these trials were: nausea (9%), insomnia (4%), somnolence (4%), headache (3%), and asthenia, vomiting, nervousness, agitation, and dizziness (2% each).

6.2 Incidence in Controlled Trials

Commonly Observed Adverse Reactions in Controlled Clinical Trials: Fluvoxamine Maleate Tablets have been studied in 10-week short-term controlled trials of OCD (N=320) and depression (N=1350). In general, adverse reaction rates were similar in the two data sets as well as in the pediatric OCD study. The most commonly observed adverse reactions associated with the use of Fluvoxamine Maleate Tablets and likely to be drug-related (incidence of 5% or greater and at least twice that for placebo) derived from Table 2 were: nausea, somnolence, insomnia, asthenia, nervousness, dyspepsia, abnormal ejaculation, sweating, anorexia, tremor, and vomiting. In a pool of two studies involving only patients with OCD, the following additional reactions were identified using the above rule: anorgasmia, decreased libido, dry mouth, rhinitis, taste perversion, and urinary frequency. In a study of pediatric patients with OCD, the following additional reactions were identified using the above rule: agitation, depression, dysmenorrhea, flatulence, hyperkinesia, and rash.

Adverse Reactions Occuring at an Incidence of 1%: Table 2 enumerates adverse reactions that occurred in adults at a frequency of 1% or more, and were more frequent than in the placebo group, among patients treated with Fluvoxamine Maleate Tablets in two short-term placebo controlled OCD trials (10 week) and depression trials (6 week) in which patients were dosed in a range of generally 100 to 300 mg/day. This table shows the percentage of patients in each group who had at least one occurrence of a reaction at some time during their treatment. Reported adverse reactions were classified using a standard COSTART-based Dictionary terminology.

The prescriber should be aware that these figures cannot be used to predict the incidence of side effects in the course of usual medical practice where patient characteristics and other factors may differ from those that prevailed in the clinical trials. Similarly, the cited frequencies cannot be compared with figures obtained from other clinical investigations involving different treatments, uses, and investigators. The cited figures, however, do provide the prescribing physician with some basis for estimating the relative contribution of drug and non-drug factors to the side-effect incidence rate in the population studied.

Adverse Reactions in OCD Placebo Controlled Studies Which are Markedly Different (defined as at least a two-fold difference) in Rate from the Pooled Reaction Rates in OCD and Depression Placebo Controlled Studies: The reactions in OCD studies with a two-fold decrease in rate compared to reaction rates in OCD and depression studies were dysphagia and amblyopia (mostly blurred vision). Additionally, there was an approximate 25% decrease in nausea.

The reactions in OCD studies with a two-fold increase in rate compared to reaction rates in OCD and depression studies were: asthenia, abnormal ejaculation (mostly delayed ejaculation), anxiety, rhinitis, anorgasmia (in males), depression, libido decreased, pharyngitis, agitation, impotence, myoclonus/twitch, thirst, weight loss, leg cramps, myalgia, and urinary retention. These reactions are listed in order of decreasing rates in the OCD trials.

6.3 Other Adverse Reactions in OCD Pediatric Population

In pediatric patients (N=57) treated with Fluvoxamine Maleate Tablets, the overall profile of adverse reactions was generally similar to that seen in adult studies, as shown in Table 2. However, the following adverse reactions, not appearing in Table 2, were reported in two or more of the pediatric patients and were more frequent with Fluvoxamine Maleate Tablets than with placebo: cough increase, dysmenorrhea, ecchymosis, emotional lability, epistaxis, hyperkinesia, manic reaction, rash, sinusitis, and weight decrease.

6.4 Male and Female Sexual Dysfunction with SSRIs

Although changes in sexual desire, sexual performance and sexual satisfaction often occur as manifestations of a psychiatric disorder and with aging, they may also be a consequence of pharmacologic treatment. In particular, some evidence suggests that selective serotonin reuptake inhibitors (SSRIs), can cause such untoward sexual experiences.

Reliable estimates of the incidence and severity of untoward experiences involving sexual desire, performance and satisfaction are difficult to obtain, however, in part because patients and physicians may be reluctant to discuss them. Accordingly, estimates of the incidence of untoward sexual experience and performance cited in product labeling are likely to underestimate their actual incidence.

Table 3 displays the incidence of sexual side effects reported by at least 2% of patients taking Fluvoxamine Maleate Tablets in placebo-controlled trials in depression and OCD.

There are no adequate and well-controlled studies examining sexual dysfunction with fluvoxamine treatment.

Fluvoxamine treatment has been associated with several cases of priapism. In those cases with a known outcome, patients recovered without sequelae and upon discontinuation of fluvoxamine.

While it is difficult to know the precise risk of sexual dysfunction associated with the use of SSRIs, physicians should routinely inquire about such possible side effects.

6.5 Vital Sign Changes

Comparisons of fluvoxamine maleate and placebo groups in separate pools of short-term OCD and depression trials on (1) median change from baseline on various vital signs variables and on (2) incidence of patients meeting criteria for potentially important changes from baseline on various vital signs variables revealed no important differences between fluvoxamine maleate and placebo.

6.6 Laboratory Changes

Comparisons of fluvoxamine maleate and placebo groups in separate pools of short-term OCD and depression trials on (1) median change from baseline on various serum chemistry, hematology, and urinalysis variables and on (2) incidence of patients meeting criteria for potentially important changes from baseline on various serum chemistry, hematology, and urinalysis variables revealed no important differences between fluvoxamine maleate and placebo.

6.7 ECG Changes

Comparisons of fluvoxamine maleate and placebo groups in separate pools of short-term OCD and depression trials on (1) mean change from baseline on various ECG variables and on (2) incidence of patients meeting criteria for potentially important changes from baseline on various ECG variables revealed no important differences between fluvoxamine maleate and placebo.

6.8 Other Reactions Observed During the Premarketing Evaluation of Fluvoxamine Maleate Tablets

During premarketing clinical trials conducted in North America and Europe, multiple doses of fluvoxamine maleate were administered for a combined total of 2737 patient exposures in patients suffering OCD or Major Depressive Disorder. Untoward reactions associated with this exposure were recorded by clinical investigators using descriptive terminology of their own choosing. Consequently, it is not possible to provide a meaningful estimate of the proportion of individuals experiencing adverse reactions without first grouping similar types of untoward reactions into a limited (i.e., reduced) number of standard reaction categories.

In the tabulations which follow, a standard COSTART-based Dictionary terminology has been used to classify reported adverse reactions. If the COSTART term for a reaction was so general as to be uninformative, it was replaced with a more informative term. The frequencies presented, therefore, represent the proportion of the 2737 patient exposures to multiple doses of fluvoxamine maleate who experienced a reaction of the type cited on at least one occasion while receiving fluvoxamine maleate. All reported reactions are included in the list below, with the following exceptions: 1) those reactions already listed in Table 2, which tabulates incidence rates of common adverse experiences in placebo-controlled OCD and depression clinical trials, are excluded; 2) those reactions for which a drug cause was not considered likely are omitted; 3) reactions for which the COSTART term was too vague to be clinically meaningful and could not be replaced with a more informative term; and 4) reactions which were reported in only one patient and judged to not be potentially serious are not included. It is important to emphasize that, although the reactions reported did occur during treatment with fluvoxamine maleate, a causal relationship to fluvoxamine maleate has not been established.

Reactions are further classified within body system categories and enumerated in order of decreasing frequency using the following definitions: frequent adverse reactions are defined as those occurring on one or more occasions in at least 1/100 patients; infrequent adverse reactions are those occurring between 1/100 and 1/1000 patients; and rare adverse reactions are those occurring in less than 1/1000 patients.

Body as a Whole – Frequent: malaise; Infrequent: photosensitivity reaction and suicide attempt.

Cardiovascular System – Frequent: syncope.

Digestive System – Infrequent: gastrointestinal hemorrhage and melena; Rare: hematemesis.

Hemic and Lymphatic Systems – Infrequent: anemia and ecchymosis; Rare: purpura.

Metabolic and Nutritional Systems – Frequent: weight gain and weight loss.

Nervous System – Frequent: hyperkinesia, manic reaction, and myoclonus; Infrequent: abnormal dreams, akathisia, convulsion, dyskinesia, dystonia, euphoria, extrapyramidal syndrome, and twitching; Rare: withdrawal syndrome.

Respiratory System – Infrequent: epistaxis. Rare: hemoptysis and laryngismus.

Skin – Infrequent: urticaria.

Urogenital System* – Infrequent: hematuria, menorrhagia, and vaginal hemorrhage; Rare: hematospermia.

* Based on the number of males or females, as appropriate.

6.9 Postmarketing Reports

Voluntary reports of adverse reactions in patients taking Fluvoxamine Maleate Tablets that have been received since market introduction and are of unknown causal relationship to Fluvoxamine Maleate Tablets use include: acute renal failure, agranulocytosis, amenorrhea, anaphylactic reaction, angioedema, aplastic anemia, bullous eruption, Henoch-Schoenlein purpura, hepatitis, ileus, pancreatitis, porphyria, Stevens-Johnson syndrome, toxic epidermal necrolysis, vasculitis, and ventricular tachycardia (including torsades de pointes).

10. OVERDOSAGE 10.1 Human Experience

Worldwide exposure to fluvoxamine includes over 45,000 patients treated in clinical trials and an estimated exposure of 50,000,000 patients treated during worldwide marketing experience (end of 2005). Of the 539 cases of deliberate or accidental overdose involving fluvoxamine reported from this population, there were 55 deaths. Of these, 9 were in patients thought to be taking fluvoxamine alone and the remaining 46 were in patients taking fluvoxamine along with other drugs. Among non-fatal overdose cases, 404 patients recovered completely. Five patients experienced adverse sequelae of overdosage, to include persistent mydriasis, unsteady gait, hypoxic encephalopathy, kidney complications (from trauma associated with overdose), bowel infarction requiring a hemicolectomy, and vegetative state. In 13 patients, the outcome was provided as abating at the time of reporting. In the remaining 62 patients, the outcome was unknown. The largest known ingestion of fluvoxamine involved 12,000 mg (equivalent to 2 to 3 months' dosage). The patient fully recovered. However, ingestions as low as 1,400 mg have been associated with lethal outcome, indicating considerable prognostic variability.

Commonly (≥5%) observed adverse events associated with fluvoxamine maleate overdose include gastrointestinal complaints (nausea, vomiting and diarrhea), coma, hypokalemia, hypotension, respiratory difficulties, somnolence, and tachycardia. Other notable signs and symptoms seen with fluvoxamine maleate overdose (single or multiple drugs) include bradycardia, ECG abnormalities (such as heart arrest, QT interval prolongation, first degree atrioventricular block, bundle branch block, and junctional rhythm), convulsions, dizziness, liver function disturbances, tremor, and increased reflexes.

10.2 Management of Overdosage

Treatment should consist of those general measures employed in the management of overdosage with any antidepressant.

Ensure an adequate airway, oxygenation, and ventilation. Monitor cardiac rhythm and vital signs. General supportive and symptomatic measures are also recommended. Induction of emesis is not recommended. Gastric lavage with a large-bore orogastric tube with appropriate airway protection, if needed, may be indicated if performed soon after ingestion, or in symptomatic patients.

Activated charcoal should be administered. Due to the large volume of distribution of this drug, forced diuresis, dialysis, hemoperfusion and exchange transfusion are unlikely to be of benefit. No specific antidotes for fluvoxamine are known.

A specific caution involves patients taking, or recently having taken, fluvoxamine who might ingest excessive quantities of a tricyclic antidepressant. In such a case, accumulation of the parent tricyclic and/or an active metabolite may increase the possibility of clinically significant sequelae and extend the time needed for close medical observation. (See DRUG INTERACTIONS [7.2].)

In managing overdosage, consider the possibility of multiple drug involvement. The physician should consider contacting a poison control center for additional information on the treatment of any overdose. Telephone numbers for certified poison control centers are listed in the Physicians’ Desk Reference (PDR).

2. DOSAGE AND ADMINISTRATION 2.1 Adults

The recommended starting dose for Fluvoxamine Maleate Tablets in adult patients is 50 mg, administered as a single daily dose at bedtime. In the controlled clinical trials establishing the effectiveness of Fluvoxamine Maleate Tablets in OCD, patients were titrated within a dose range of 100 to 300 mg/day. Consequently, the dose should be increased in 50 mg increments every 4 to 7 days, as tolerated, until maximum therapeutic benefit is achieved, not to exceed 300 mg per day. It is advisable that a total daily dose of more than 100 mg should be given in two divided doses. If the doses are not equal, the larger dose should be given at bedtime.

2.2 Pediatric Population (children and adolescents)

The recommended starting dose for Fluvoxamine Maleate Tablets in pediatric populations (ages 8-17 years) is 25 mg, administered as a single daily dose at bedtime. In a controlled clinical trial establishing the effectiveness of Fluvoxamine Maleate Tablets in OCD, pediatric patients (ages 8-17) were titrated within a dose range of 50 to 200 mg/day. Physicians should consider age and gender differences when dosing pediatric patients. The maximum dose in children up to age 11 should not exceed 200 mg/day. Therapeutic effect in female children may be achieved with lower doses. Dose adjustment in adolescents (up to the adult maximum dose of 300 mg) may be indicated to achieve therapeutic benefit. The dose should be increased in 25 mg increments every 4 to 7 days, as tolerated, until maximum therapeutic benefit is achieved. It is advisable that a total daily dose of more then 50 mg should be given in two divided doses. If the two divided doses are not equal, the larger dose should be given at bedtime.

2.3 Elderly or Hepatically Impaired Patients

Elderly patients and those with hepatic impairment have been observed to have a decreased clearance of fluvoxamine maleate. Consequently, it may be appropriate to modify the initial dose and the subsequent dose titration for these patient groups.

2.4 Pregnant Women During the Third Trimester

Neonates exposed to Fluvoxamine Maleate Tablets and other SSRIs or SNRIs late in the third trimester have developed complications requiring prolonged hospitalization, respiratory support, and tube feeding and may be at risk for persistent pulmonary hypertension of the newborn (PPHN). (See USE IN SPECIFIC POPULATIONS [8.1].) When treating pregnant women with Fluvoxamine Maleate Tablets during the third trimester, the physician should carefully consider the potential risks and benefits of treatment. The physician may consider tapering Fluvoxamine Maleate Tablets in the third trimester.

2.5 Switching Patients To or From a Monoamine Oxidase Inhibitor

At least 14 days should elapse between discontinuation of an MAOI and initiation of therapy with Fluvoxamine Maleate Tablets. Similarly, at least 14 days should be allowed after stopping Fluvoxamine Maleate Tablets before starting an MAOI.

2.6 Maintenance/Continuation Extended Treatment

It is generally agreed that obsessive compulsive disorder requires several months or longer of sustained pharmacologic therapy. The benefit of maintaining patients with OCD on Fluvoxamine Maleate Tablets after achieving a response for an average duration of about 4 weeks in a 10-week single-blind phase during which patients were titrated to effect was demonstrated in a controlled trial [see CLINICAL TRIALS (14.2)]. The physician who elects to use Fluvoxamine Maleate Tablets for extended periods should periodically re-evaluate the long-term usefulness of the drug for the individual patient.

2.7 Discontinuation of Treatment with Fluvoxamine Maleate Tablets

Symptoms associated with discontinuation of other SSRIs or SNRIs have been reported. (See WARNINGS AND PRECAUTIONS [5.8].) Patients should be monitored for these symptoms when discontinuing treatment. A gradual reduction in the dose rather than abrupt cessation is recommended whenever possible. If intolerable symptoms occur following a decrease in the dose or upon discontinuation of treatment, then resuming the previously prescribed dose may be considered. Subsequently, the physician may continue decreasing the dose but at a more gradual rate.

HOW SUPPLIED

16. HOW SUPPLIED/STORAGE AND HANDLING 16.1 How Supplied

Fluvoxamine Maleate Tablets are available in the following strengths, colors, imprints, and presentations:

Tablets 25 mg: unscored, white, elliptical, film-coated (debossed “1222” on one side)

Bottles of 100......................................................................................NDC 42769-1222-0

Tablets 50 mg: scored, yellow, elliptical, film-coated (debossed “1225” on one side and scored on the other)

Bottles of 100......................................................................................NDC 42769-1225-0

Tablets 100 mg: scored, beige, elliptical, film-coated (debossed “1221” on one side and scored on the other)

Bottles of 100......................................................................................NDC 42769-1221-0

16.2 Storage

Keep out of reach of children.

Fluvoxamine Maleate Tablets should be protected from high humidity and stored at 25°C (77°F); excursions permitted to 15° to 30°C (59° to 86°F) [see USP Controlled Room Temperature].

Dispense in tight containers.

17. PATIENT COUNSELING INFORMATION

Prescribers or other health professionals should inform patients, their families, and their caregivers about the benefits and risks associated with treatment with Fluvoxamine Maleate Tablets and should counsel them in the appropriate use. A patient Medication Guide about “Antidepressant Medicines, Depression and other Serious Mental Illnesses, and Suicidal Thoughts or Actions” is available for Fluvoxamine Maleate Tablets. The prescriber or health professional should instruct patients, their families, and their caregivers to read the Medication Guide and should assist them in understanding its contents. Patients should be given the opportunity to discuss the contents of the Medication Guide and to obtain answers to any questions they may have. The complete text of the Medication Guide is reprinted at the end of this document.

Patients should be advised of the following issues and asked to alert their prescriber if these occur while taking Fluvoxamine Maleate Tablets.

17.1 Clinical Worsening and Suicide Risk

Patients, their families, and their caregivers should be encouraged to be alert to the emergence of anxiety, agitation, panic attacks, insomnia, irritability, hostility, aggressiveness, impulsivity, akathisia (psychomotor restlessness), hypomania, mania, other unusual changes in behavior, worsening of depression, and suicidal ideation, especially early during antidepressant treatment and when the dose is adjusted up or down. Families and caregivers of patients should be advised to look for the emergence of such symptoms on a day-to-day basis, since changes may be abrupt. Such symptoms should be reported to the patient’s prescriber or health professional, especially if they are severe, abrupt in onset, or were not part of the patient’s presenting symptoms. Symptoms such as these may be associated with an increased risk for suicidal thinking and behavior and indicate the need for very close monitoring and possibly changes in the medication (see Boxed Warning and WARNINGS AND PRECAUTIONS [5.1]).

17.2 Serotonin Syndrome

Patients should be cautioned about the risk of serotonin syndrome with the concomitant use of fluvoxamine and triptans, tramadol, or other serotonergic agents (see WARNINGS AND PRECAUTIONS-Serotonergic Drugs [5.7]).

17.3 Interference with Cognitive or Motor Performance

Since any psychoactive drug may impair judgment, thinking, or motor skills, patients should be cautioned about operating hazardous machinery, including automobiles, until they are certain that Fluvoxamine Maleate Tablets therapy does not adversely affect their ability to engage in such activities.

17.4 Pregnancy

Patients should be advised to notify their physicians if they become pregnant or intend to become pregnant during therapy with Fluvoxamine Maleate Tablets (see USE IN SPECIFIC POPULATIONS [8.1]).

17.5 Nursing

Patients receiving Fluvoxamine Maleate Tablets should be advised to notify their physicians if they are breast-feeding an infant. (See USE IN SPECIFIC POPULATIONS - Nursing Mothers [8.3].)

17.6 Concomitant Medication

Patients should be advised to notify their physicians if they are taking, or plan to take, any prescription or over-the-counter drugs, since there is a potential for clinically important interactions with Fluvoxamine Maleate Tablets.

Patients should be cautioned about the concomitant use of fluvoxamine and NSAIDs, aspirin, or other drugs that affect coagulation since the combined use of psychotropic drugs that interfere with serotonin reuptake and these agents has been associated with an increased risk of bleeding (see WARNINGS AND PRECAUTIONS-Warfarin and Other Drugs That Interfere With Hemostasis [5.7]).

Because of the potential for the increased risk of serious adverse reactions including severe lowering of blood pressure and sedation when fluvoxamine and tizanidine are used together, fluvoxamine should not be used with tizanidine (see WARNINGS AND PRECAUTIONS [5.4]).

Because of the potential for the increased risk of serious adverse reactions when fluvoxamine and alosetron are used together, fluvoxamine should not be used with LotronexTM (alosetron) (see WARNINGS AND PRECAUTIONS [5.6]).

17.7 Alcohol

As with other psychotropic medications, patients should be advised to avoid alcohol while taking Fluvoxamine Maleate Tablets.

17.8 Allergic Reactions

Patients should be advised to notify their physicians if they develop a rash, hives, or a related allergic phenomenon during therapy with Fluvoxamine Maleate Tablets.

LotronexTM is a registrered trademark of GlaxoSmithKline.

Manufactured for

BayPharma, Inc.

Baltimore, MD 21244

BOXED WARNING

Suicidality and Antidepressant Drugs

Antidepressants increased the risk compared to placebo of suicidal thinking and behavior (suicidality) in children, adolescents, and young adults in short-term studies of major depressive disorder (MDD) and other psychiatric disorders. Anyone considering the use of Fluvoxamine Maleate Tablets or any other antidepressant in a child, adolescent, or young adult must balance this risk with the clinical need. Short-term studies did not show an increase in the risk of suicidality with antidepressants compared to placebo in adults beyond age 24; there was a reduction in risk with antidepressants compared to placebo in adults aged 65 and older. Depression and certain other psychiatric disorders are themselves associated with increases in the risk of suicide. Patients of all ages who are started on antidepressant therapy should be monitored appropriately and observed closely for clinical worsening, suicidality, or unusual changes in behavior. Families and caregivers should be advised of the need for close observation and communication with the prescriber. Fluvoxamine Maleate Tablets are not approved for use in pediatric patients except for patients with obsessive compulsive disorder (OCD). (See WARNINGS AND PRECAUTIONS-Clinical Worsening and Suicide Risk [5.1].)

PACKAGE LABEL

fluvoxamine 25mg